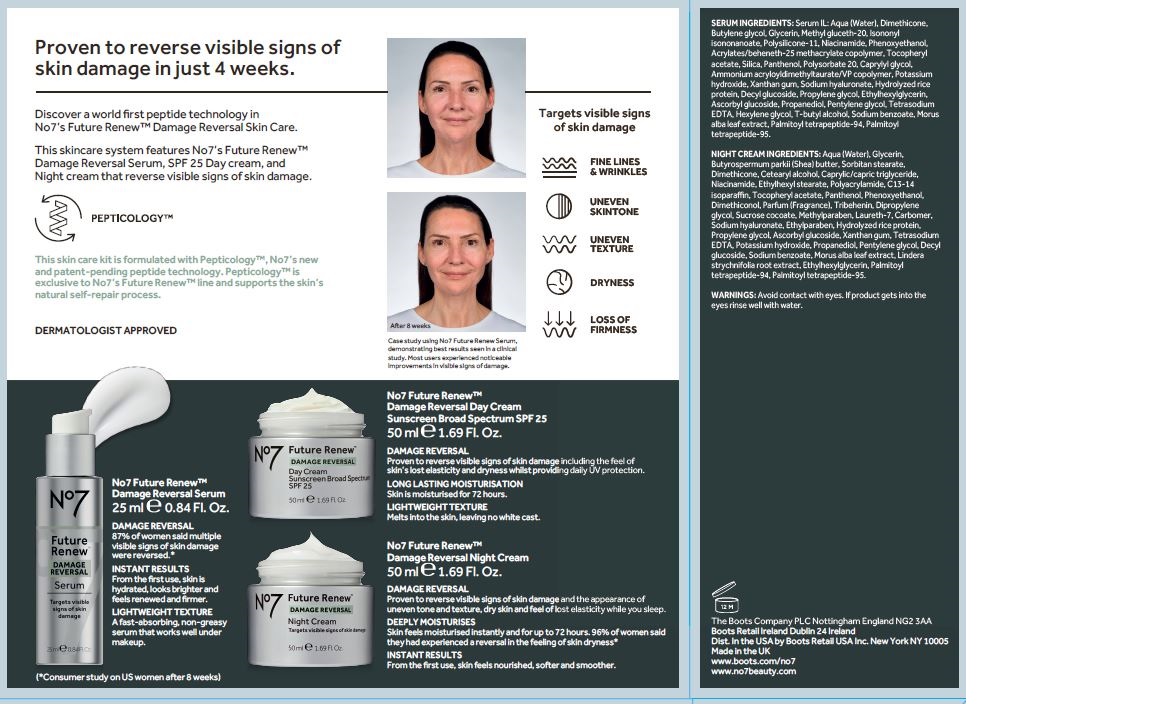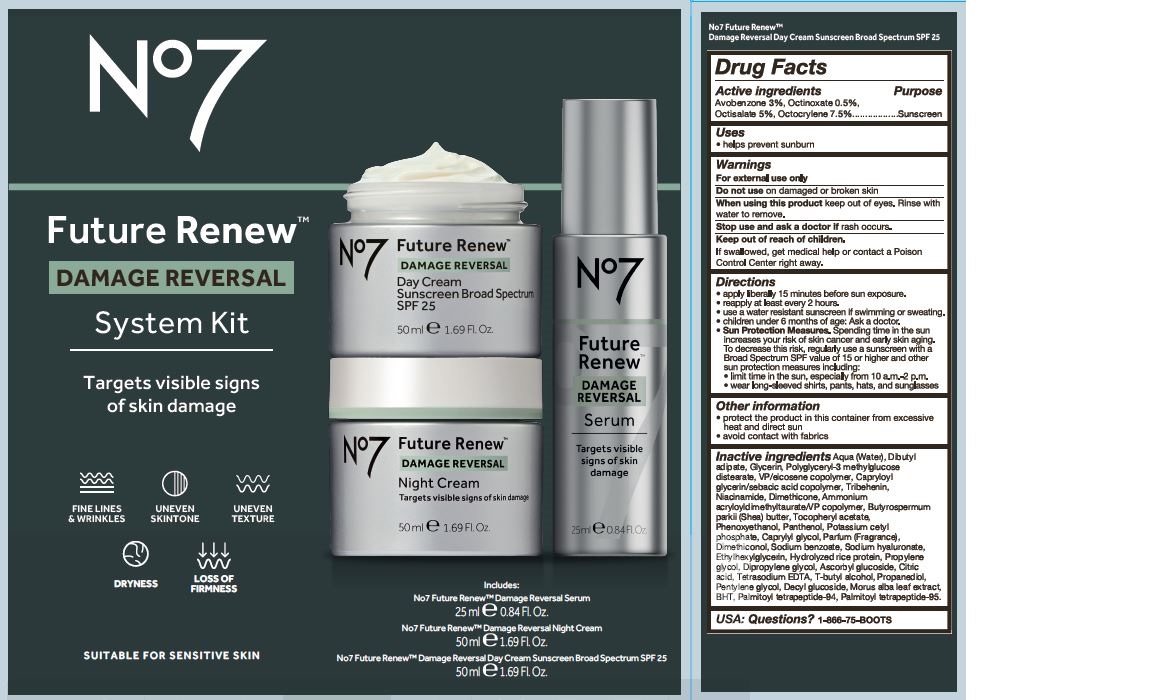 DRUG LABEL: No7 Future Renew Damage Reversal System Kit
NDC: 61589-9720 | Form: CREAM
Manufacturer: BCM Cosmetique SAS
Category: otc | Type: HUMAN OTC DRUG LABEL
Date: 20250722

ACTIVE INGREDIENTS: AVOBENZONE 1.5 g/50 g; OCTINOXATE 0.25 g/50 g; OCTOCRYLENE 3.75 g/50 g; OCTISALATE 2.5 g/50 g
INACTIVE INGREDIENTS: WATER; DIBUTYL ADIPATE; GLYCERIN; POLYGLYCERYL-3 METHYLGLUCOSE DISTEARATE; CAPRYLOYL GLYCERIN/SEBACIC ACID COPOLYMER (2000 MPA.S); TRIBEHENIN; DIMETHICONE; NIACINAMIDE; POTASSIUM CETYL PHOSPHATE; AMMONIUM ACRYLOYLDIMETHYLTAURATE/VP COPOLYMER; PHENOXYETHANOL; SHEA BUTTER; PANTHENOL; CAPRYLYL GLYCOL; DIMETHICONOL (40 CST); PROPYLENE GLYCOL; DIPROPYLENE GLYCOL; .ALPHA.-TOCOPHEROL ACETATE, D-; SODIUM BENZOATE; HYALURONATE SODIUM; ASCORBYL GLUCOSIDE; ETHYLHEXYLGLYCERIN; TERT-BUTYL ALCOHOL; CITRIC ACID ACETATE; EDETATE SODIUM; PROPANEDIOL; PENTYLENE GLYCOL; DECYL GLUCOSIDE; MORUS ALBA LEAF; BUTYLATED HYDROXYTOLUENE; PALMITOYL TETRAPEPTIDE-94; PALMITOYL TETRAPEPTIDE-95; VINYLPYRROLIDONE/EICOSENE COPOLYMER

No7 Future Renew Damage Reversal System Kit with No 7 Future Renew Damage Reversal Day Cream Sunscreen Broad Spectrum SPF 25

Carton Active Ingredients Section

Active ingredients

Avobenzone 3%

Octinoxate 0.5%

Octisalate 5%

Octocrylene 7.5%

Uses

Uses - helps prevent sunburn

Warnings

For external use only

Do not use on damaged or broken skin

When using this product keep out of eyes. Rinse with water to remove.

Ask a doctor

Stop use and ask a doctor if rash occurs

Keep out of reach of children

If swallowed, get medical help or contact a Poison Control Center right away

Directions

apply liberally 15 minutes before sun exposure.

reapply at least every 2 hours.

use a water resistant sunscreen if swimming or sweating.

children under 6 months of age: Ask a doctor.

Sun Protection Measures. Spending time in the sun increases your risk of skin cancer and early skin aging. To decrease this risk, regularly use a sunscreen with a Broad Spectrum SPF value of 15 or higher and other sun protection measures including:

limit time in the sun, especially from 10 a.m-2 p.m.

wear long-sleeved shirts, pants, hats and sunglasses

Directions

apply liberally 15 minutes before sun exposure.

reapply at least every 2 hours.

use a water resistant sunscreen if swimming or sweating.

children under 6 months of age: Ask a doctor.

Sun Protection Measures. Spending time in the sun increases your risk of skin cancer and early skin aging. To decrease this risk, regularly use a sunscreen with a Broad Spectrum SPF value of 15 or higher and other sun protection measures including:

limit time in the sun, especially from 10 a.m-2 p.m.

wear long-sleeved shirts, pants, hats and sunglasses

Storage

Other information

protect the product in this container from excessive heat and direct sun

avoid contact with fabrics

Inactive ingredients

Aqua (Water), Dibutyl adipate, Glycerin, Polyglyceryl-3 methylglucose distearate, VP/eicosene copolymer, Capryloyl glycerin/sebacic acid copolymer, Tribehenin, Niacinamide, Dimethicone, Ammonium acryloyldimethyltaurate/VP copolymer, Butyrospermum parkii (Shea) butter, Tocopheryl acetate, Phenoxyethanol, Panthenol, Potassium cetyl phosphate, Caprylyl glycol, Parfum (fragrance), Dimethiconol, Sodium Benzoate, Sodium Hyaluronate, Ethylhexylglycerin, Hydrolyzed rice protein, Propylene glycol, Dipropylene glycol, Ascorbyl glucoside, Citric acid, Tetrasodium EDTA, T-butyl alcohol, Propanediol, Pentylene Glycol, Decyl glucoside, Morus alba leaf extract, BHT, Palmitoyl tetrapeptide-94, Palmitoyl tetrapeptide-95

PATIENT COUNSELING INFORMATION

USA: Questions? 1-866-75-BOOTS

The Boots Company PLC Nottingham England NG2 3AA

Boots Retail Ireland Dublin 12 Ireland

Dist. in the USA by Boots Retail USA Inc. New York NY 10007

Made in the UK

www.no7beauty.com